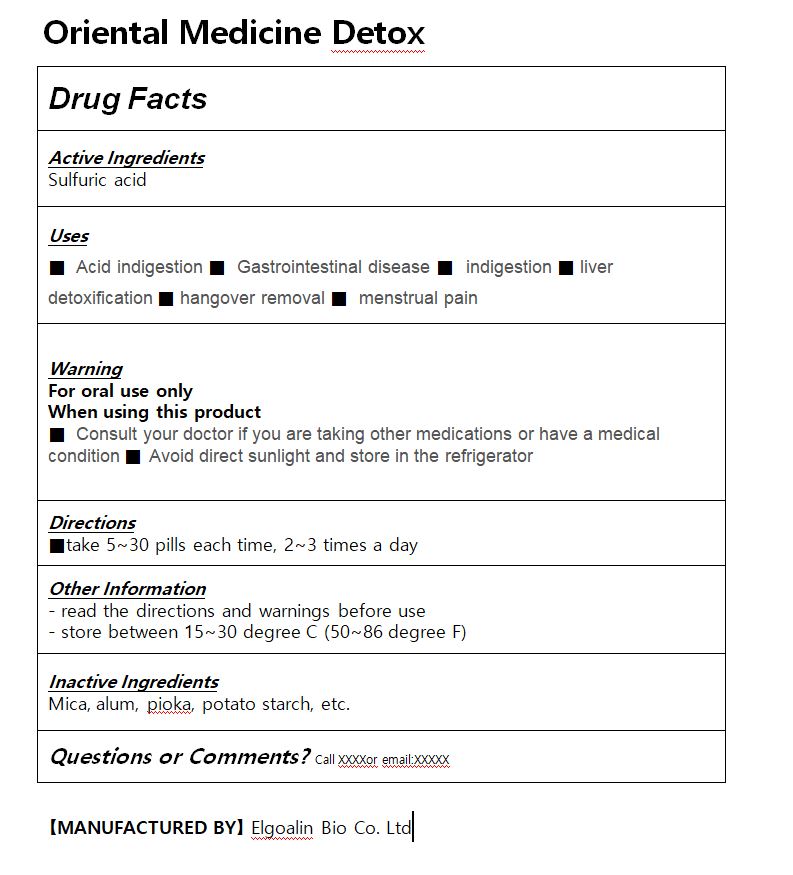 DRUG LABEL: Oriental Medicine Detox
NDC: 82677-0003 | Form: PILL
Manufacturer: Elgoalin Bio Co.,Ltd
Category: homeopathic | Type: HUMAN OTC DRUG LABEL
Date: 20220425

ACTIVE INGREDIENTS: SULFURIC ACID 0.5 g/1 1
INACTIVE INGREDIENTS: STARCH, TAPIOCA; MICA

ACTIVE INGREDIENT

sulfuric acid

INACTIVE INGREDIENT

Mica, alum, pioka, potato starch, etc.

PURPOSE

■ Acid indigestion ■ Gastrointestinal disease ■ indigestion ■ liver detoxification ■ hangover removal ■ menstrual pain

keep out of reach of the children

INDICATIONS AND USAGE

Take 500ml each time, 3 times a day

WARNINGS

Consult your doctor if you are taking other medications or have a medical condition
Avoid direct sunlight and store in the refrigerator

DOSAGE AND ADMINISTRATION

for oral use only